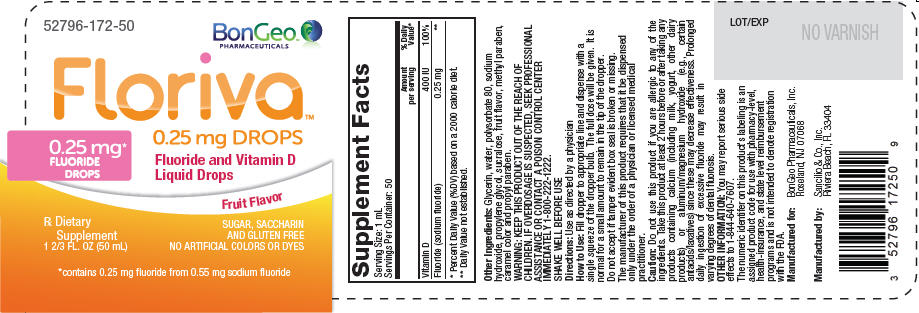 DRUG LABEL: Floriva
NDC: 52796-172 | Form: LIQUID
Manufacturer: BonGeo Pharmaceuticals, Inc.
Category: prescription | Type: HUMAN PRESCRIPTION DRUG LABEL
Date: 20240201

ACTIVE INGREDIENTS: CHOLECALCIFEROL 400 [iU]/1 mL; SODIUM FLUORIDE 0.25 mg/1 mL
INACTIVE INGREDIENTS: GLYCERIN; WATER; POLYSORBATE 80; SODIUM HYDROXIDE; PROPYLENE GLYCOL; SUCRALOSE; METHYLPARABEN; PROPYLPARABEN

Floriva™
0.25 mg DROPS

DESCRIPTION

Supplement Facts
Serving Size: 1 mL
Servings Per Container: 50
 | Amount per serving | % Daily Value [Percent Daily Value (%DV) based on a 2000 calorie diet.]
Vitamin D | 400 IU | 100%
Fluoride (sodium fluoride) | 0.25 mg | [Daily Value not established.]

Other Ingredients: Glycerin, water, polysorbate 80, sodium hydroxide, propylene glycol, sucralose, fruit flavor, methyl paraben, caramel color and propyl paraben.

WARNING

KEEP THIS PRODUCT OUT OF THE REACH OF CHILDREN. IF OVERDOSAGE IS SUSPECTED, SEEK PROFESSIONAL ASSISTANCE OR CONTACT A POISON CONTROL CENTER IMMEDIATELY 1-800-222-1222.

SHAKE WELL BEFORE USE

Directions

Use as directed by a physician

How to Use

Fill dropper to appropriate line and dispense with a single squeeze of the dropper bulb. The full dose will be given. It is normal for a small amount to remain in the tip of the dropper.

Do not accept if tamper evident box seal is broken or missing.

The manufacturer of this product requires that it be dispensed only under the order of a physician or licensed medical practitioner.

Caution

Do not use this product if you are allergic to any of the ingredients. Take this product at least 2 hours before or after taking any products containing calcium (including milk, yogurt, other dairy products) or aluminum/magnesium hydroxide (e.g., certain antacids/laxatives) since these may decrease effectiveness. Prolonged daily ingestion of excessive fluoride may result in varying degrees of dental fluorosis.

OTHER INFORMATION

You may report serious side effects to 1-844-640-7607.

The numeric identifer on this product's labeling is an assigned product code for use with pharmacy-level, health-insurance, and state level reimbursement programs and is not intended to denote registration with the FDA.

Manufactured for:
BonGeo Pharmaceuticals, Inc.
Roseland, NJ 07068

Manufactured by:
Sancilio & Co., Inc.
Riviera Beach, FL 33404

LOT/EXP

PRINCIPAL DISPLAY PANEL - 50 mL Bottle Label

52796-172-50

BonGeo™
PHARMACEUTICALS

Floriva™
0.25 mg DROPS

0.25 mg*
FLUORIDE
DROPS

Fluoride and Vitamin D
Liquid Drops

Fruit Flavor

Rx Dietary
Supplement
1 2/3 FL. OZ (50 mL)

SUGAR, SACCHARIN
AND GLUTEN FREE
NO ARTIFICIAL COLORS OR DYES

*contains 0.25 mg fluoride from 0.55 mg sodium fluoride